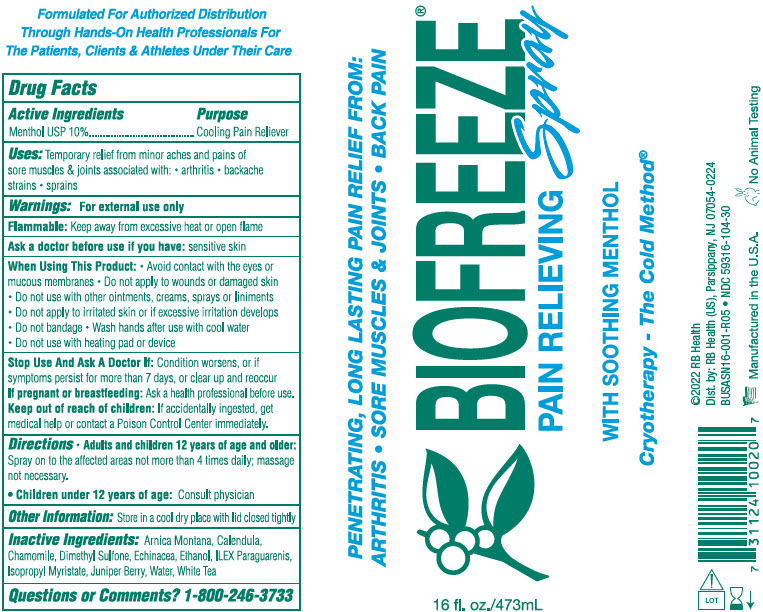 DRUG LABEL: Biofreeze
NDC: 59316-104 | Form: SPRAY
Manufacturer: RB Health (US) LLC
Category: otc | Type: HUMAN OTC DRUG LABEL
Date: 20250703

ACTIVE INGREDIENTS: MENTHOL, UNSPECIFIED FORM 100 mg/1 mL
INACTIVE INGREDIENTS: ARNICA MONTANA WHOLE; CALENDULA OFFICINALIS FLOWER; CHAMOMILE; DIMETHYL SULFOXIDE; ECHINACEA, UNSPECIFIED; ALCOHOL; ILEX PARAGUARIENSIS LEAF; ISOPROPYL MYRISTATE; JUNIPERUS COMMUNIS WHOLE; WATER

Biofreeze Pain Relieving Spray

Active Ingredients:

Menthol USP 10%

Purpose

Cooling Pain Reliever

Uses:

Temporary relief from minor aches and pains of sore muscles and joints associated with: -arthritis - backache - strains - sprains

Warnings:

For external use only

Flammable: Keep away from excessive heat or open flame

Ask a doctor before use if you have:

sensitive skin

When Using This Product:

-Avoid contact with the eyes or mucous membranes - Do not apply to wounds or damages skin -Do not use with other ointments, creams, sprays or liniments -Do not apply to irritated skin or if excessive irritation develops -Do not bandage - Wash hands after use with cool water -Do not use with heating pad or device

Stop Use And Ask A Doctor If:

Condition worsens, or if symptoms persist for more than 7 days, or clear up and reoccur

If pregnant or breastfeeding:

Ask a health professional before use.

Keep out of reach of children:

If accidentally ingested, get medical help or contact a Poison Control Center immediately.

Directions

Adults and children 12 years of age and older:Spray on to the affected areas not more than 4 times daily; massage not necessary.

Children under 12 years of age:Consult a physician

Other Information:

Store in a cool dry place with lid closed tightly

Inactive Ingredients:

Arnica Montana, Calendula,Chamomile, Dimethyl Sulfone, Echinacea, Ethanol, ilex Paraguarenis, Isopropyl Myristate, Juniper Berry, water, White Tea

Questions or Comments?

1-800-246-3733

Dist. by: RB Health (US), Parsippany, NJ 07054-0224

PRINCIPAL DISPLAY PANEL - 473 mL Bottle Label

PENETRATING, LONG LASTING PAIN RELIEF FROM:
ARTHRITIS • SORE MUSCLES & JOINTS • BACK PAIN

BIOFREEZE®
PAIN RELIEVING Spray

WITH SOOTHING MENTHOL

Cryotherapy - The Cold Method®

16 fl. oz./473mL